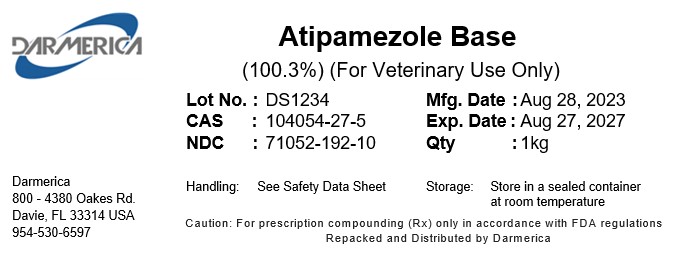 DRUG LABEL: Atipamezole Base
NDC: 71052-192 | Form: POWDER
Manufacturer: DARMERICA, LLC
Category: other | Type: BULK INGREDIENT - ANIMAL DRUG
Date: 20250722

ACTIVE INGREDIENTS: ATIPAMEZOLE 1 kg/1 kg

Atipamezole Base